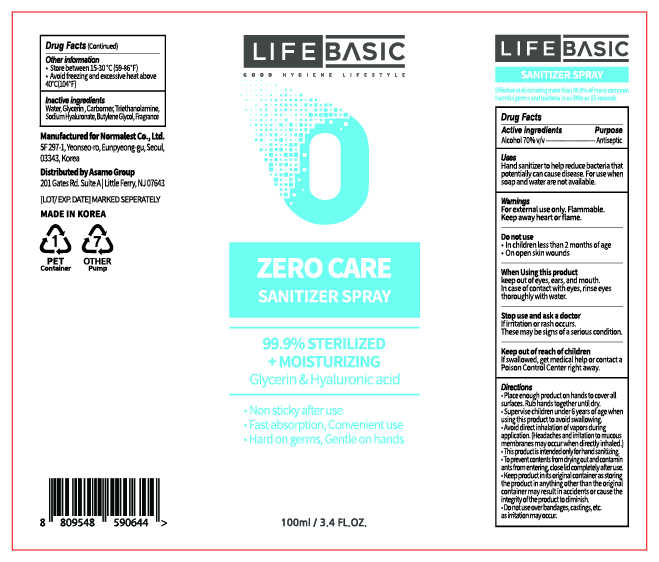 DRUG LABEL: LIFEBASIC ZERO CARE SANITIZERspray
NDC: 72284-7100 | Form: SPRAY
Manufacturer: Normalest Co., Ltd.
Category: otc | Type: HUMAN OTC DRUG LABEL
Date: 20200517

ACTIVE INGREDIENTS: ALCOHOL 70 mL/100 mL
INACTIVE INGREDIENTS: GLYCERIN; CARBOMER HOMOPOLYMER, UNSPECIFIED TYPE; WATER; BUTYLENE GLYCOL; HYALURONATE SODIUM; TROLAMINE

LIFEBASIC ZERO CARE SANITIZER SPRAY 100 ml : 72284-7100